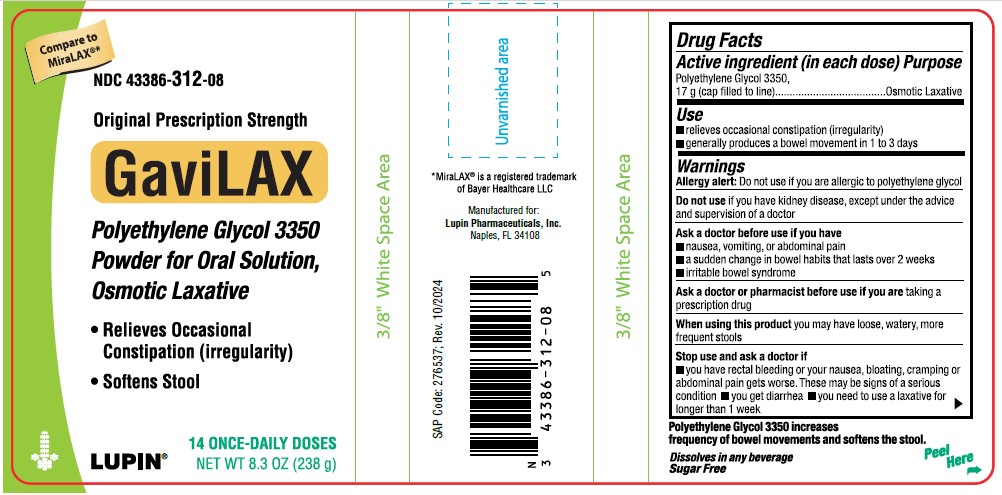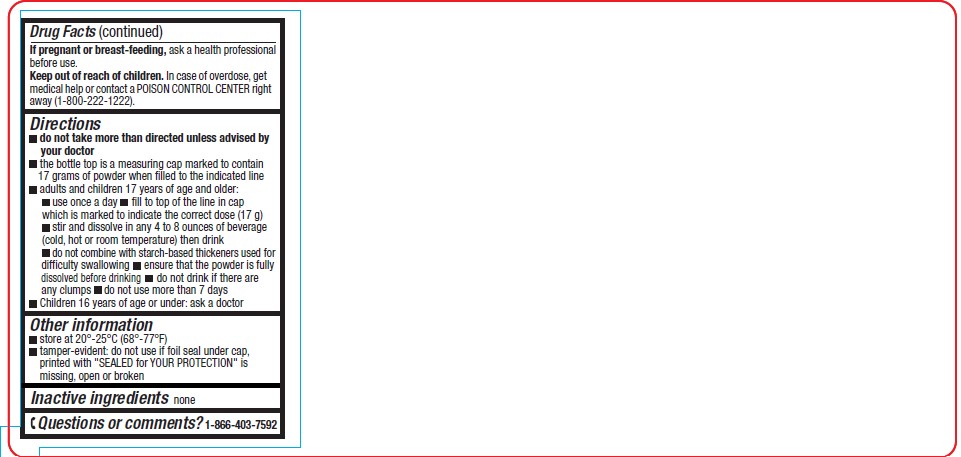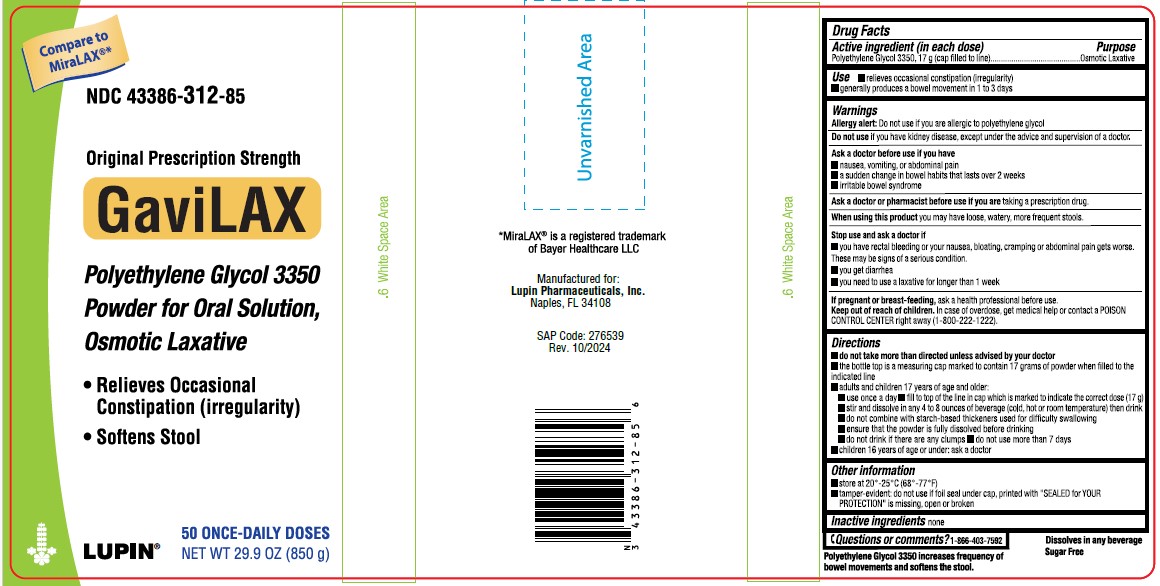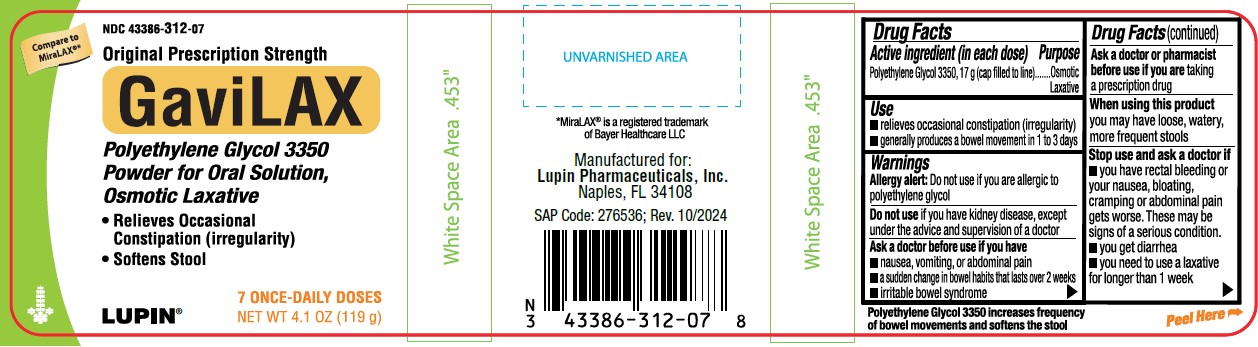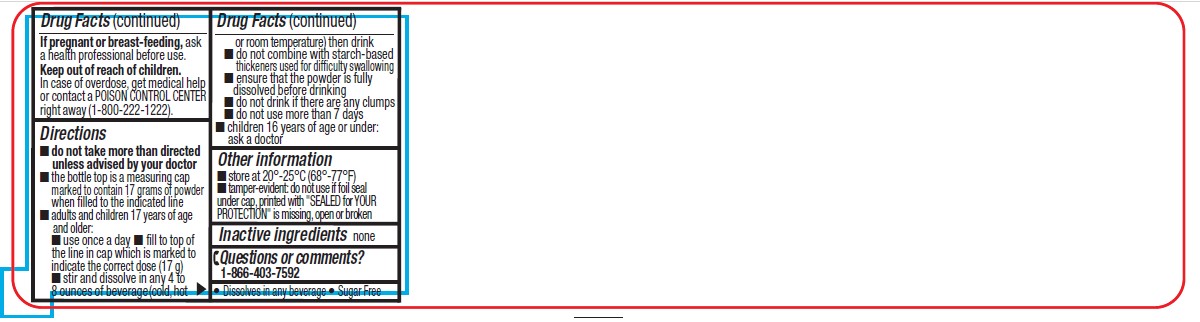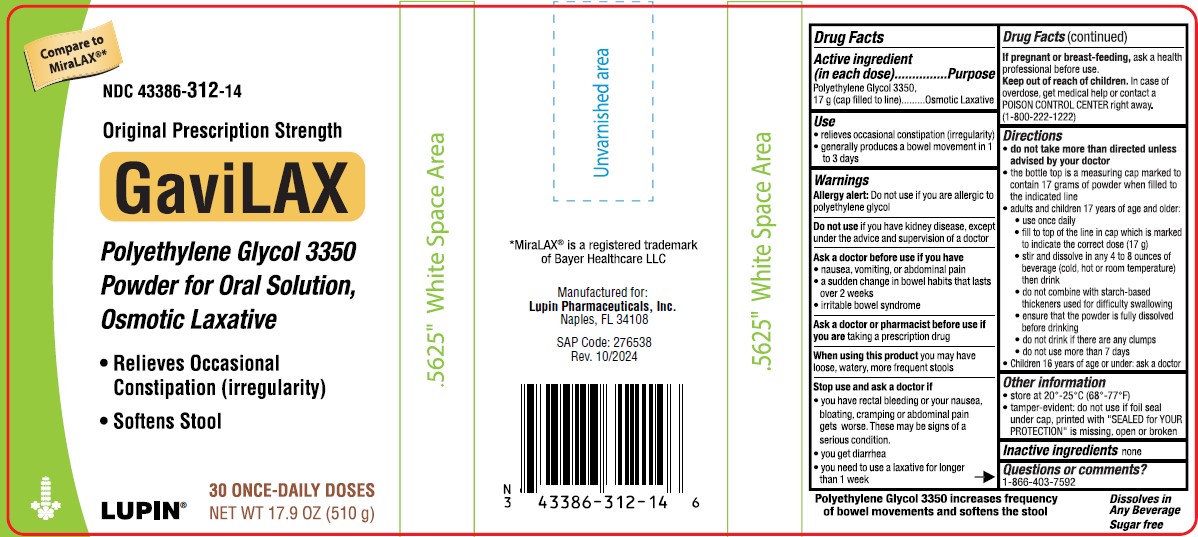 DRUG LABEL: GAVILAX
NDC: 43386-312 | Form: POWDER, FOR SOLUTION
Manufacturer: Lupin Pharmaceuticals,Inc.
Category: otc | Type: HUMAN OTC DRUG LABEL
Date: 20251208

ACTIVE INGREDIENTS: POLYETHYLENE GLYCOL 3350 17 g/17 g
INACTIVE INGREDIENTS: SODIUM HYDROXIDE

Drug Facts

Active Ingredient

Polyethylene Glycol 3350, 17 g (cap filled to line)……………………Osmotic Laxative

Purpose

Use

- relieves occasional constipation (irregularity)
- generally produces a bowel movement in 1 to 3 days

WARNINGS

Allergy alert: Do not use if you are allergic to polyethylene glycol

Do not use if you have kidney disease, except under the advice and supervision of a doctor

Ask a doctor before use if you have

- nausea, vomiting or abdominal pain
- a sudden change in bowel habits that lasts over 2 weeks
- irritable bowel syndrome

Ask a doctor or pharmacist before use if you are taking a prescription drug

When using this product you may have loose, watery, more frequent stools

Stop use and ask a doctor if

- you have rectal bleeding or your nausea, bloating, cramping or abdominal pain gets worse. These may be signs of a serious condition.
- you get diarrhea
- you need to use a laxative for longer than 1 week

If pregnant or breast-feeding, ask a health professional before use.

Keep out of the reach of children

In case of overdose, get medical help or contact a POISON CONTROL CENTER right away. (1-800-222-1222)

Directions

- do not take more than directed unless advised by your doctor
- the bottle top is a measuring cap marked to contain 17 grams of powder when filled to the indicated line.
- adults and children 17 years of age and older:
- use once a day
- fill to top of line in cap which is marked to indicate the correct dose (17 g)
- stir and dissolve in any 4 to 8 ounces of beverage (cold, hot or room temperature) then drink
- do not combine with starch-based thickeners used for difficulty swallowing
- ensure that the powder is fully dissolved before drinking
- do not drink if there are any clumps
- do not use more than 7 days
- children 16 years of age or under: ask a doctor

Other Information

- store at 20°- 25°C (68°– 77°F)
- tamper-evident: do not use if printed foil seal under cap, printed with "SEALED for YOUR PROTECTION" is missing, open or broken

Inactive Ingredient

none

Questions or comments?

1-866-403-7592

- Dissolves in any beverages
- Sugar Free

PACKAGE LABEL.PRINCIPAL DISPLAY PANEL

NDC 43386-312-08

Original Prescription Strength

GaviLax

Polyethylene Glycol 3350

Powder for Oral Solution, Osmotic Laxative

14 ONCE-DAILY DOSES

NET WT 8.3 OZ (238 g)

NDC 43386-312-85

Original Prescription Strength

GaviLax

Polyethylene Glycol 3350

Powder for Oral Solution, Osmotic Laxative

50 ONCE-DAILY DOSES

NET WT 29.9 OZ (850 g)

NDC 43386-312-07

Original Prescription Strength

GaviLax

Polyethylene Glycol 3350

Powder for Oral Solution, Osmotic Laxative

7 ONCE-DAILY DOSES

NET WT 4.1 OZ (119 g)

NDC 43386-312-14

Original Prescription Strength

GaviLax

Polyethylene Glycol 3350

Powder for Oral Solution, Osmotic Laxative

30 ONCE-DAILY DOSES

NET WT 17.9 OZ (510 g)